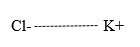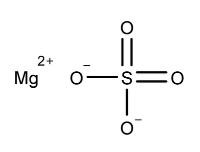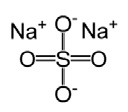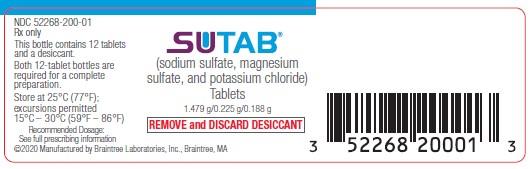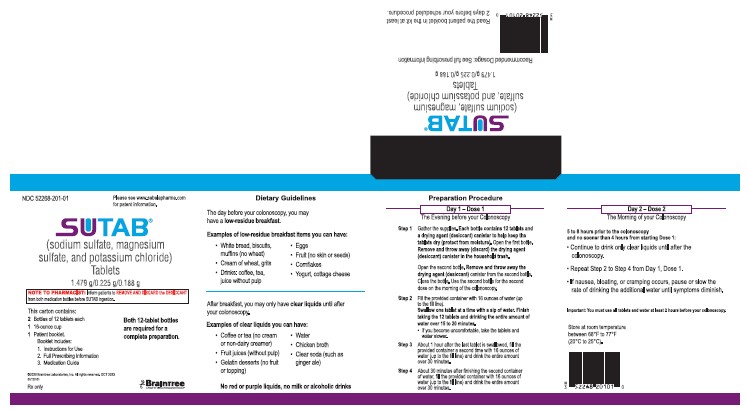 DRUG LABEL: SUTAB
NDC: 52268-201 | Form: TABLET
Manufacturer: Braintree Laboratories, Inc.
Category: prescription | Type: HUMAN PRESCRIPTION DRUG LABEL
Date: 20231103

ACTIVE INGREDIENTS: SODIUM SULFATE 17.75 g/1 1; MAGNESIUM SULFATE ANHYDROUS 2.7 g/1 1; POTASSIUM CHLORIDE 2.25 g/1 1
INACTIVE INGREDIENTS: POLYETHYLENE GLYCOL 8000; SODIUM CAPRYLATE; ETHYLENE GLYCOL; POLYVINYL ALCOHOL GRAFT POLYETHYLENE GLYCOL COPOLYMER (3:1; 45000 MW)

HIGHLIGHTS OF PRESCRIBING INFORMATION

These highlights do not include all the information needed to use
SUTAB®safely and effectively. See full prescribing information for
SUTAB.
SUTAB (sodium sulfate, magnesium sulfate, and potassium chloride)
tablets, for oral use
Initial U.S. Approval: 2020

RECENT MAJOR CHANGES

Dosage and Administration (2.1, 2.2) | 10/2023
Warnings and Precautions (5.8) | 10/2023

1 INDICATIONS AND USAGE

SUTAB is an osmotic laxative indicated for cleansing of the colon in preparation for colonoscopy in adults.

2 DOSAGE AND ADMINISTRATION

For complete information on preparation before colonoscopy and administration of the dosage regimen, see full prescribing information. (2.1, 2.2)

Preparation and Administration (2.1)

- Administration of two doses (24 tablets) are required for a complete preparation for colonoscopy.
- SUTAB is supplied as two bottles each containing 12 tablets. Twelve (12) tablets are equivalent to one dose.
- Each SUTAB bottle contains a desiccant. Remove and discard the desiccantfrom both bottles the evening prior to the colonoscopy.
- Must consume water with each dose and an additional 32 ounces of water after each dose.
- Do not take other laxatives.
- Administer oral medications at least 1 hour before starting each dose of SUTAB.
- If taking tetracycline or fluoroquinolone antibiotics, iron, digoxin, chlorpromazine, or penicillamine, take these medications at least 2 hours before and not less than 6 hours after administration of each dose.

Recommended Split Dose (2-Day) Regimen (2.2)

Day 1, Dose 1: On the Evening Prior to Colonoscopy

1. Open 1 bottle of 12 tablets. Remove and discard the desiccant. Remove and discard the desiccantfrom the second bottle and close the bottle. Use the second bottle for the second dose on the morning of the colonoscopy.
2. Fill the provided container with 16 ounces of water (up to the fill line). Swallow each tablet with a sip of water and drink the entire amount over 15 to 20 minutes.
3. Approximately one hour after the last tablet is ingested, fill the provided container a second time with 16 ounces of water (up to the fill line) and drink the entire amount over 30 minutes.
4. Approximately 30 minutes after finishing the second container of water, fill the provided container with 16 ounces of water (up to the fill line) and drink the entire amount over 30 minutes.

Day 2, Dose 2: Morning of the Colonoscopy (5 to 8 hours prior to the colonoscopy and no sooner than 4 hours from starting Dose 1):

- Continue to consume only clear liquids until after the colonoscopy.
- Repeat Step 2 to Step 4 from Day 1, Dose 1.
- If patients experience preparation-related symptoms (e.g., nausea, bloating, cramping), pause or slow the rate of drinking the additional water until symptoms diminish.
- Complete all SUTAB tablets and water at least two hours prior to colonoscopy.

3 DOSAGE FORMS AND STRENGTHS

Tablets: 1.479 g sodium sulfate, 0.225 g magnesium sulfate, and 0.188 g potassium chloride.

4 CONTRAINDICATIONS

- Gastrointestinal obstruction or ileus (4, 5.6)
- Bowel perforation (4, 5.6)
- Toxic colitis or toxic megacolon (4)
- Gastric retention (4)
- Hypersensitivity to any ingredient in SUTAB (4, 5.7)

5 WARNINGS AND PRECAUTIONS

- Risk of fluid and electrolyte abnormalities: Encourage adequate hydration, assess concurrent medications and consider laboratory assessments prior to and after each use. (5.1, 7.1)
- Cardiac arrhythmias: Consider pre-dose and post-colonoscopy ECGs in patients at increased risk. (5.2)
- Seizures: Use caution in patients with a history of seizures and patients at increased risk of seizures, including medications that lower the seizure threshold. (5.3, 7.1)
- Patients with renal impairment or taking concomitant medications that affect renal function: Use caution, ensure adequate hydration and consider laboratory testing. (5.4, 7.1)
- Colonic Mucosal ulcerations: Consider potential for mucosal ulcerations when interpreting colonoscopy findings in patients with known or suspected inflammatory bowel disease. (5.5)
- Suspected GI obstruction or perforation: Rule out the diagnosis before administration. (4, 5.6)
- Hypersensitivity reactions, including anaphylaxis: Inform patients to seek immediate medical care if symptoms occur. (5.7)
- Risk of Gastrointestinal Complications with Ingestion of Desiccant: Postmarketing reports of ingestion of the desiccant along with SUTAB tablets has been reported and may be associated with risk of gastrointestinal complications and/or choking. (2.2, 5.8)

6 ADVERSE REACTIONS

Most common gastrointestinal adverse reactions are nausea, abdominal distension, vomiting and upper abdominal pain. (6.1)
To report SUSPECTED ADVERSE REACTIONS, contact Braintree Laboratories, Inc. at 1-800-874-6756 or FDA at 1-800-FDA-1088 orwww.fda.gov/medwatch.

7 DRUG INTERACTIONS

Drugs that increase risk of fluid and electrolyte imbalance (7.1)

FULL PRESCRIBING INFORMATION

1 INDICATIONS AND USAGE

SUTAB is indicated for the cleansing of the colon as a preparation for colonoscopy in adults.

2 DOSAGE AND ADMINISTRATION

2.1 Important Preparation and Administration Instructions

- Correct fluid and electrolyte abnormalities before treatment with SUTAB [see Warnings and Precautions (5.1)]
- Administration of two doses of SUTAB (24 tablets) are required for a complete preparation for colonoscopy.
- SUTAB is supplied as two bottles each containing 12 tablets. Twelve (12) tablets are equivalent to one dose.
- Each SUTAB bottle contains a desiccant. Remove and discard the desiccantfrom both bottles of SUTAB the evening prior to the colonoscopy [see Dosage and Administration (2.2)] .
- Must consume water with each dose of SUTAB and an additional 32 ounces of water must be consumed after each dose [see Dosage and Administration (2.2) and Warnings and Precautions (5.1)] .
- Consume a low residue breakfast on the day before colonoscopy, followed by clear liquids up to 2 hours prior to colonoscopy.
- Do not drink milk or eat or drink anything colored red or purple.
- Do not drink alcohol.
- Do not take other laxatives while taking SUTAB.
- Administer oral medications at least 1 hour before starting each dose of SUTAB.
- If taking tetracycline or fluoroquinolone antibiotics, iron, digoxin, chlorpromazine, or penicillamine, take these medications at least 2 hours before and not less than 6 hours after administration of each dose of SUTAB.
- Stop consumption of all fluids at least 2 hours prior to the colonoscopy.

2.2 Recommended Split-Dose (2-Day) Dosage Regimen

The recommended Split-Dose (2-day) dosage regimen for adults consists of two doses of SUTAB: the first dose during the evening prior to colonoscopy and the second dose the next day, during the morning of the colonoscopy.

Instruct patients:

On the Day Prior to Colonoscopy:

- A low residue breakfast may be consumed. Examples of low residue foods are eggs, white bread, cottage cheese, yogurt, grits, coffee, tea.
- After breakfast, only clear liquids may be consumed until after the colonoscopy. Examples of clear liquids are coffee or tea (no cream or non-dairy creamer), fruit juices (without pulp), gelatin desserts (no fruit or topping), water, chicken broth, clear soda (such as ginger ale).

Day 1, Dose 1 - On the Evening Prior to Colonoscopy:

1. Early in the evening prior to colonoscopy, open one bottle of 12 tablets. Remove and discard the desiccant.Remove and discard the desiccant from the second bottle and close the bottle. Use the second bottle for the second dose on the morning of the colonoscopy.
2. Fill the provided container with 16 ounces of water (up to the fill line). Swallow one tablet at a time with a sip of water. Finish taking the 12 tablets and drinking the entire amount of water within 15 to 20 minutes.
3. Approximately one hour after the last tablet is ingested, fill the provided container a second time with 16 ounces of water (up to the fill line) and drink the entire amount over 30 minutes.
4. Approximately 30 minutes after finishing the second container of water, fill the provided container again with 16 ounces of water (up to the fill line) and drink the entire amount over 30 minutes.

If patients experience preparation-related symptoms (e.g. nausea, bloating, cramping), pause or slow the rate of drinking the additional water until symptoms diminish.

Day 2, Dose 2 – The Morning of the Colonoscopy(5 to 8 hours prior to the colonoscopy and no sooner than 4 hours from starting Dose 1):

- Continue to consume only clear liquids until after the colonoscopy.
- Repeat Step 2 to Step 4 from Day 1, Dose 1.
- If patients experience preparation-related symptoms (e.g., nausea, bloating, cramping), pause or slow the rate of drinking the additional water until symptoms diminish.
- Complete taking all SUTAB tablets and water at least two hours prior to colonoscopy.

3 DOSAGE FORMS AND STRENGTHS

Tablets: 1.479 g sodium sulfate, 0.225 g magnesium sulfate, and 0.188 g potassium chloride. The tablets are white to off-white, film coated, oblong, and biconvex with flat sides, debossed with S24on one side.

4 CONTRAINDICATIONS

SUTAB is contraindicated in the following conditions:

- Gastrointestinal obstruction or ileus [see Warnings and Precautions (5.6)
- Bowel Perforation [see Warnings and Precautions (5.6)
- Toxic colitis or toxic megacolon
- Gastric retention
- Hypersensitivity to any ingredient in SUTAB [see Warnings and Precautions (5.7) and Description (11)]

5 WARNINGS AND PRECAUTIONS

5.1 Serious Fluid and Electrolyte Abnormalities

Advise all patients to hydrate adequately before, during, and after the use of SUTAB. If a patient develops significant vomiting or signs of dehydration after taking SUTAB, consider performing postcolonoscopy lab tests (electrolytes, creatinine, and BUN). Fluid and electrolyte disturbances can lead to serious adverse events including cardiac arrhythmias, seizures and renal impairment. Correct fluid and electrolyte abnormalities before treatment with SUTAB. Use SUTAB with caution in patients with conditions, or who are using medications, that increase the risk for fluid and electrolyte disturbances or may increase the risk of adverse events of seizure, arrhythmias, and renal impairment [see Drug Interactions (7.1)] .

5.2 Cardiac Arrhythmias

There have been rare reports of serious arrhythmias associated with the use of ionic osmotic laxative products for bowel preparation. Use caution when prescribing SUTAB for patients at increased risk of arrhythmias (e.g., patients with a history of prolonged QT, uncontrolled arrhythmias, recent myocardial infarction, unstable angina, congestive heart failure, or cardiomyopathy). Consider predose and post-colonoscopy ECGs in patients at increased risk of serious cardiac arrhythmias.

5.3 Seizures

There have been reports of generalized tonic-clonic seizures and/or loss of consciousness associated with use of bowel preparation products in patients with no prior history of seizures. The seizure cases were associated with electrolyte abnormalities (e.g., hyponatremia, hypokalemia, hypocalcemia, and hypomagnesemia) and low serum osmolality. The neurologic abnormalities resolved with correction of fluid and electrolyte abnormalities.

Use caution when prescribing SUTAB for patients with a history of seizures and in patients at increased risk of seizure, such as patients taking medications that lower the seizure threshold (e.g., tricyclic antidepressants), patients withdrawing from alcohol or benzodiazepines, or patients with known or suspected hyponatremia [see Drug Interactions (7.1)] .

5.4 Use in Patients with Risk of Renal Injury

Use SUTAB with caution in patients with impaired renal function or patients taking concomitant medications that may affect renal function (such as diuretics, angiotensin converting enzyme inhibitors, angiotensin receptor blockers, or non-steroidal anti-inflammatory drugs) [see Drug Interactions (7.1)] . These patients may be at risk for renal injury. Advise these patients of the importance of adequate hydration with SUTAB and consider performing baseline and postcolonoscopy laboratory tests (electrolytes, creatinine, and BUN) in these patients [see Use in Specific Populations (8.6)] .

5.5 Colonic Mucosal Ulcerations and Ischemic Colitis

Osmotic laxative products may produce colonic mucosal aphthous ulcerations, and there have been reports of more serious cases of ischemic colitis requiring hospitalization. Concurrent use of stimulant laxatives and SUTAB may increase these risks [see Drug Interactions (7.3)] . Consider the potential for mucosal ulcerations resulting from the bowel preparation when interpreting colonoscopy findings in patients with known or suspect inflammatory bowel disease (IBD).

5.6 Use in Patients with Significant Gastrointestinal Disease

If gastrointestinal obstruction or perforation is suspected, perform appropriate diagnostic studies to rule out these conditions before administering SUTAB [see Contraindications (4)] .

Use in caution in patients with severe active ulcerative colitis.

5.7 Hypersensitivity Reactions

Serious hypersensitivity reactions, including anaphylaxis, angioedema, dyspnea, rash, pruritis and urticaria have been reported with SUTAB [see Adverse Reactions (6.2)] . Inform patients of the signs and symptoms of anaphylaxis and instruct them to seek immediate medical care should signs and symptoms occur.

6 ADVERSE REACTIONS

The following serious or otherwise important adverse reactions for bowel preparations are described elsewhere in the labeling:

- Serious Fluid and Electrolyte Abnormalities [see Warnings and Precautions (5.1)]
- Cardiac Arrhythmias [see Warnings and Precautions (5.2)]
- Seizures [see Warnings and Precautions (5.3)]
- Patients with Risk of Renal Injury [see Warnings and Precautions (5.4)]
- Colonic Mucosal Ulceration and Ischemic Colitis [see Warnings and Precautions (5.5)]
- Patients with Significant Gastrointestinal Disease [see Warnings and Precautions (5.6)]
- Hypersensitivity Reactions [see Warnings and Precautions (5.7)]
- Risk of Gastrointestinal Complications with Ingestion of Desiccant [see Warnings and Precautions (5.8)]

6.1 Clinical Trials Experience

Because clinical studies are conducted under widely varying conditions, adverse reaction rates observed in the clinical studies of a drug cannot be directly compared to rates in clinical studies of another drug and may not reflect the rates observed in practice.

The safety of SUTAB was evaluated in two randomized, parallel group, multicenter, investigator blinded clinical trials in 941 adult patients undergoing colonoscopy. The active comparators were polyethylene glycol 3350, sodium sulfate, sodium chloride, potassium chloride, ascorbic acid and sodium ascorbate for oral solution in Study 1 and sodium picosulfate, magnesium oxide, and anhydrous citric acid for oral solution in Study 2 [see Clinical Studies (14)] .

Adverse Gastrointestinal Reactions Reported by Symptom Questionnaire
In Studies 1 and 2, patients were queried for selected gastrointestinal adverse reactions of stomach cramping (upper abdominal pain), stomach bloating (abdominal distention), nausea and vomiting using a standard questionnaire following completion of study drug and prior to colonoscopy on the day of colonoscopy. Patients reporting selected gastrointestinal symptom(s) rated the intensity as mild, moderate or severe.

A total of 52% (287/552) of patients in Study 1 and 52% (202/389) in Study 2 reported at least one selected gastrointestinal adverse reaction when queried using the standard questionnaire. Tables 1 and 2 show results for each gastrointestinal adverse reaction reported by patients using the standard questionnaire, including severity.

Table 1: Gastrointestinal Symptoms by SeverityaFrom Symptom Questionnaire in Adult Patients Following Colon Cleansing and Prior to Colonoscopy – Study 1b
Symptom | SUTAB | Polyethylene glycol 3350, sodium sulfate, sodium chloride, potassium chloride, ascorbic acid and sodium ascorbate
Total Number or Patients per Treatment Arm (N) | 281 | 271
Patients with at Least One Gastrointestinal Adverse Reaction from Symptom Questionnaire | 163 | 124
% Nauseac | 48 | 26
Mild | 71 | 77
Moderate | 27 | 23
Severe | 2 | 0
% Abdominal Distensionc,d | 29 | 22
Mild | 68 | 71
Moderate | 30 | 29
Severe | 1 | 0
% Vomitingc | 23 | 5
Mild | 48 | 46
Moderate | 52 | 54
Severe | 0 | 0
% Upper Abdominal Painc | 16 | 18
Mild | 65 | 71
Moderate | 35 | 29
Severe | 0 | 0
Total Number of Patients per Treatment Arm (N) | 281 | 271
a Mild: barely noticeable, does not influence functioning causing no limitations of usual activities;
Moderate: makes participant uncomfortable, influences functioning causing some limitations of usual activities;
Severe: severe discomfort, treatment needed, severe and undesirable, causing inability to carry out usual activities
bStudy 1 was not designed to support comparative claims for SUTAB for the adverse reactions reported in this table.
cPercentage represents n/N for patients who experienced each gastrointestinal adverse reaction on the symptom questionnaire based on the total number of patients per treatment arm.

Table 2: Gastrointestinal Symptoms by SeverityaFrom Symptom Questionnaire in Adult Patients Following Colon Cleansing and Prior to Colonoscopy – Study 2b
Symptom | SUTAB | Sodium picosulfate, magnesium oxide, and anhydrous citric acid
Total Number or Patients per Treatment Arm (N) | 190 | 199
Patients with at Least One Gastrointestinal Adverse Reaction from Symptom Questionnaire | 135 | 67
% Nauseac | 52 | 18
Mild | 74 | 94
Moderate | 20 | 6
Severe | 6 | 0
% Abdominal Distensionc | 34 | 15
Mild | 73 | 69
Moderate | 27 | 31
Severe | 0 | 0
% Vomitingc | 16 | 2
Mild | 53 | 33
Moderate | 47 | 67
Severe | 0 | 0
% Upper Abdominal Painc | 23 | 13
Mild | 82 | 100
Moderate | 16 | 0
Severe | 2 | 0
Total Number of Patients per Treatment Arm (N) | 190 | 199
Patients with at Least One Gastrointestinal Adverse Reaction from Symptom Questionnaire | 135 | 67
a Mild: barely noticeable, does not influence functioning causing no limitations of usual activities;
Moderate: makes participant uncomfortable, influences functioning causing some limitations of usual activities;
Severe: severe discomfort, treatment needed, severe and undesirable, causing inability to carry out usual activities
bStudy 2 was not designed to support comparative claims for SUTAB for the adverse reactions reported in this table.
cPercentage represents n/N for patients who experienced each gastrointestinal adverse reaction on the symptom questionnaire based on the total number of patients per treatment arm.

Additional Adverse Reactions Reported in Studies 1 and 2
In addition to the gastrointestinal symptoms reported on the standard questionnaire (Tables 1 and 2), other adverse reactions reported in at least 2% of patients in either treatment arm in Studies 1 and 2 were: dizziness in Study 1 (0% SUTAB and 2% comparator); and hypermagnesemia (2% SUTAB and 2% comparator) and increased liver function test (including ALT, AST and bilirubin) (3% SUTAB and 1% comparator) in Study 2.

Laboratory Changes
Electrolyte Abnormalities
Shifts in serum electrolytes from normal at baseline to above the upper end of normal following study drug on the day of colonoscopy in at least 2% of patients in either treatment arm and at least 2% greater in patients treated with SUTAB than treated with comparator in either Study 1 or Study 2 were: magnesium (27% SUTAB and 5% comparator in Study 1), and serum osmolality (44% SUTAB and 28% comparator in Study 2). These changes were transient and resolved without intervention.

Renal Function Parameters
Decreases in creatinine clearance and increases in blood urea nitrogen (BUN) were reported in less than 1% of patients in both SUTAB and comparator arms in both trials.

6.2 Postmarketing Experience

The following adverse reactions have been identified during post-approval use of SUTAB. Because these reactions are reported voluntarily from a population of uncertain size, it is not always possible to reliably estimate their frequency or establish a causal relationship to drug exposure.

Gastrointestinal: gastric ulceration, gastritis

Hypersensitivity: anaphylaxis, angioedema, dyspnea, rash, pruritus, urticaria [see Warnings and Precautions (5.7)]

7 DRUG INTERACTIONS

7.1 Drugs That May Increase Risks of Fluid and Electrolyte Abnormalities

Use caution when prescribing SUTAB to patients taking medications that increase the risk of fluid and electrolyte disturbances or may increase the risk of adverse events of seizure, arrhythmias, and prolonged QT in the setting of fluid and electrolyte abnormalities [see Warnings and Precautions (5.1, 5.2, 5.3, 5.4)] .

7.2 Potential for Reduced Drug Absorption

SUTAB can reduce the absorption of other co-administered drugs [see Dosage and Administration (2.1)] :

- Administer oral medications at least one hour before starting each dose of SUTAB.
- Administer tetracycline and fluoroquinolone antibiotics, iron, digoxin, chlorpromazine, and penicillamine at least 2 hours before and not less than 6 hours after administration of each dose of SUTAB to avoid chelation with magnesium.

7.3 Stimulant Laxatives

Concurrent use of stimulant laxatives and SUTAB may increase the risk of mucosal ulceration or ischemic colitis. Avoid use of stimulant laxatives (e.g., bisacodyl, sodium picosulfate) while taking SUTAB [see Warnings and Precautions (5.5)] .

8 USE IN SPECIFIC POPULATIONS

8.1 Pregnancy

Risk Summary

There are no available data on SUTAB use in pregnant women to evaluate for a drug-associated risk of major birth defects, miscarriage, or adverse maternal or fetal outcomes. No reproduction or developmental studies in animals have been conducted with sodium sulfate, magnesium sulfate, and potassium chloride (SUTAB).

The estimated background risk of major birth defects and miscarriage for the indicated population is unknown. All pregnancies have a background risk of birth defect, loss, or other adverse outcomes. In the U.S. general population, the estimated background risk of major birth defects and miscarriage in clinically recognized pregnancies is 2% to 4% and 15% to 20%, respectively.

8.2 Lactation

Risk Summary

There are no available data on the presence of SUTAB in human or animal milk, the effects of on the breastfed child, or the effects on milk production.

The developmental and health benefits of breastfeeding should be considered along with the mother’s clinical need for SUTAB and any potential adverse effects on the breastfed child from SUTAB or from the underlying maternal condition.

8.4 Pediatric Use

Safety and effectiveness in pediatric patients have not been established.

8.5 Geriatric Use

Of the 471 patients who received SUTAB in pivotal clinical trials, 150 (32%) were 65 years of age or older, and 25 (5%) were 75 years of age or older. No differences in safety or effectiveness of SUTAB were observed between geriatric patients and younger patients. Elderly patients are more likely to have decreased hepatic, renal or cardiac function and may be more susceptible to adverse reactions resulting from fluid and electrolyte abnormalities [see Warnings and Precautions (5.1)] .

8.6 Renal Impairment

Use SUTAB with caution in patients with renal impairment or patients taking concomitant medications that may affect renal function. These patients may be at risk for renal injury. Advise these patients of the importance of adequate hydration before, during and after use of SUTAB and consider performing baseline and post-colonoscopy laboratory tests (electrolytes, creatinine, and BUN) in these patients [see Warning and Precautions (5.4)] .

10 OVERDOSAGE

Overdosage of more than the recommended dose of SUTAB may lead to severe electrolyte disturbances, as well as dehydration and hypovolemia, with signs and symptoms of these disturbances [see Warnings and Precautions (5.1, 5.2, 5.3)] . Monitor for fluid and electrolyte disturbances and treat symptomatically.

11 DESCRIPTION

SUTAB (sodium sulfate, magnesium sulfate, and potassium chloride) tablets is an orally administered osmotic laxative and is provided as two bottles, each containing 12 tablets. Each tablet contains: 1.479 g sodium sulfate, 0.225 g magnesium sulfate, and 0.188 g potassium chloride. Inactive ingredients include: polyethylene glycol 8000, sodium caprylate, and ethylene glycol and vinyl alcohol graft copolymer.

Sodium Sulfate, USP

The molecular formula is Na2SO4. The average molecular weight is 142.04. The structural formula is:

Magnesium Sulfate, USP

The molecular formula is MgSO4. The average molecular weight is 120.37. The structural formula is:

Potassium Chloride, USP

The molecular formula is KCl. The average molecular weight is 74.55. The structural formula is:

12 CLINICAL PHARMACOLOGY

12.1 Mechanism of Action

The primary mode of action is osmotic action of sodium sulfate and magnesium sulfate, which induce a laxative effect. The physiological consequence is increased water retention in the lumen of the colon, resulting in loose stools.

12.3 Pharmacokinetics

Absorption
After the oral administration of SUTAB to patients in clinical studies, the median serum sulfate concentration increased by about 2.5-fold at 5 to 8 hours post Dose 2 (0.61 mmol/L) compared to baseline (0.25 mmol/L) and returned to baseline by 24 to 48 hours after colonoscopy.

Elimination
Fecal excretion is the primary route of sulfate elimination.

Use in Specific Populations
Patients with Renal Impairment
The disposition of sulfate after ingestion of a sulfate-based product containing sodium sulfate, potassium sulfate, and magnesium sulfate similar to SUTAB was studied in patients (N=6) with moderate renal impairment (creatinine clearance of 30 to 49 mL/min). In patients with moderate renal impairment, mean AUC was 54% higher and mean Cmax was 44% higher than healthy subjects. The mean sulfate concentrations in healthy subjects and in patients with moderate renal impairment returned to their respective baselines by Day 6 after dose initiation. Urinary excretion of sulfate over 30 hours after the first dose was approximately 16% lower in patients with moderate renal impairment than in healthy subjects. These differences are not considered clinically meaningful.

Patients with Hepatic Impairment
The disposition of sulfate after ingestion of a sulfate-based product containing sodium sulfate, potassium sulfate, and magnesium sulfate similar to SUTAB was also studied in patients (N=6) with mild-moderate hepatic impairment (Child-Pugh grades A and B). Systemic exposure of serum sulfate (AUC and Cmax) was similar between healthy subjects and patients with hepatic impairment. The mean sulfate concentrations in healthy subjects and in patients with mild to moderate hepatic impairment returned to their respective baselines by Day 6 after dose initiation. Urinary excretion of sulfate over 30 hours after the first dose was similar between patients with hepatic impairment and healthy subjects.

13 NONCLINICAL TOXICOLOGY

13.2 Animal Toxicology and/or Pharmacology

Animal toxicology studies with sodium sulfate, magnesium sulfate, and potassium chloride (SUTAB) have not been conducted. Sulfate salts of sodium, potassium, and magnesium, were administered orally (gavage) to rats and dogs up to 28 days up to a maximum daily dose of 5 grams/kg/day (approximately 0.9 and 3 times for rats and dogs, respectively, the recommended SUTAB human dose of 45.4 grams/day or 0.86 grams/kg based on the body surface area). In rats, the sulfate salts caused diarrhea and electrolyte and metabolic changes, including hypochloremia, hypokalemia, hyponatremia, lower serum osmolality, and high serum bicarbonate. Significant renal changes included increased fractional sodium excretion, increased urinary sodium and potassium excretion, and alkaline urine in both male and females. In addition, creatinine clearance was significantly decreased in females at the highest dose. No microscopic renal changes were seen. In dogs, the sulfate salts caused emesis, excessive salivation, excessive drinking of water, and abnormal excreta (soft and/or mucoid feces and/or diarrhea) and increased urine pH and sodium excretion.

14 CLINICAL STUDIES

The colon cleansing efficacy of SUTAB was evaluated in two randomized, single-blind, active-controlled, multicenter trials (Study 1 and Study 2). These trials included adult subjects undergoing colonoscopy for colorectal cancer screening and surveillance, or diagnostic colonoscopy, including subjects with abdominal pain, diarrhea, constipation and non-severe inflammatory bowel disease.

In Study 1 (BLI4700-301; NCT 03404401), 548 adult patients were included in the efficacy analysis. Patients ranged in age from 19 to 84 years (median age 59 years) and 56% were female. Racial distribution was 78% Caucasian, 16% African-American, and 11% Hispanic or Latino. Patients were randomized to one of the following two colon preparation regimens: SUTAB or polyethylene glycol 3350, sodium sulfate, sodium chloride, potassium chloride, ascorbic acid and sodium ascorbate for oral solution. Both preparations were administered according to a split-dose regimen [see Dosage and Administration (2.2)] . Patients receiving SUTAB were limited to a low residue breakfast followed by clear liquids on the day prior to the day of colonoscopy; patients receiving the comparator bowel prep were allowed to have a normal breakfast and a light lunch, followed by clear liquids and/or yogurt for dinner. Approximately 97% of patients in the study completed both doses of preparation (98% of SUTAB patients and 95% of comparator patients).

In Study 2 (BLI4700-302; NCT 03261960), 388 adult patients were included in the efficacy analysis. Patients ranged in age from 23 to 83 years (median age 58 years) and 58% were female. Racial distribution was 94% Caucasian, 9% Hispanic or Latino, and 5% African-American. Patients were randomized to one of the following two colon preparation regimens: SUTAB or sodium picosulfate, magnesium oxide, and anhydrous citric acid for oral solution. Both preparations were administered according to a split-dose regimen [see Dosage and Administration (2.2)] . Patients receiving SUTAB were limited to a low residue breakfast followed by clear liquids on the day prior to the day of colonoscopy; patients receiving the comparator bowel prep were only allowed clear liquids on the day prior to colonoscopy. Approximately 98% of patients in the study completed both doses of preparation (98% of SUTAB patients and 99% of comparator patients).

The primary efficacy endpoint in each trial was the proportion of patients with successful colon cleansing, as assessed by the blinded colonoscopist utilizing the four-point scaled described below. Success was defined as an overall cleansing assessment of 3 (Good) or 4 (Excellent).

Score | Grade | Description
1 | Poor | Large amount of fecal residue, additional bowel preparation required.
2 | Fair | Enough feces even after washing and suctioning to prevent clear visualization of the entire colonic mucosa.
3 | Good | Feces and fluid requiring washing and suctioning, but still achieves clear visualization of the entire colonic mucosa.
4 | Excellent | No more than small bits of feces/fluid which can be suctioned easily; achieves clear visualization of the entire colonic mucosa.

Results for the primary endpoint in Studies 1 and 2 are shown in Table 3. In both trials, SUTAB was non-inferior to the comparator.

Table 3 Proportion of Adult Patients with Overall Cleansing Successain Two Controlled Trials with a Split-Dose Regimen
 | SUTAB; % (n/N) | Comparator; % (n/N) | SUTAB-comparator
 |  |  | Differenceb(%) | 99% Confidence; Intervalb
Study 1 | 92%; (257/278) | 89%c; (241/270) | 3.0 | (-3.2, 9.3)e
Study 2 | 92%; (175/190) | 88%d; (174/198) | 3.1 | (-4.5, 10.7)e
aSuccess was defined as an overall cleaning assessment of 3 (Good) or 4 (Excellent) by the blinded endoscopist, scores were assigned on withdrawal of colonoscope.
btreatment differences and confidence intervals were adjusted by study sites based on Mantel-Haenszel method
ccomparator in Study 1 was polyethylene glycol 3350, sodium sulfate, sodium chloride, potassium chloride, sodium ascorbate and ascorbic acid for oral solution
dcomparator in Study 2 was sodium picosulfate, magnesium oxide, and anhydrous citric acid for oral solution
enon-inferior

16 HOW SUPPLIED/STORAGE AND HANDLING

Each tablet of SUTAB contains 1.479 g sodium sulfate, 0.225 g magnesium sulfate, and 0.188 g potassium chloride. The tablets are white to off-white, film coated, oblong, and biconvex with flat sides, debossed with S24 on one side.

Each carton of SUTAB (NDC 52268-201-01) contains:

- Two bottles, each bottle (NDC 52268-200-01) contains 12 tablets.
- One container with a 16-ounce fill line.

Note to Pharmacist: Inform the patient to removeand discardthe desiccant from both bottles of SUTAB the evening prior to the colonoscopy [see Dosage and Administration (2.2)]

Storage
Store at 20º to 25°C (68º to 77°F). Excursions permitted between 15º to 30°C (59º to 86°F). See USP controlled room temperature.

17 PATIENT COUNSELING INFORMATION

Advise the patient to read the FDA-approved patient labeling (Medication Guide and Instructions for Use).

Instruct patients:

- Administration of two doses of SUTAB (24 tablets) are required for a complete preparation for colonoscopy.
- SUTAB is supplied as two bottles each containing 12 tablets. Twelve (12) tablets are equivalent to one dose.
- Each SUTAB bottle contains a desiccant. Remove and discard the desiccantfrom both bottles of SUTAB the evening prior to the colonoscopy [see Dosage and Administration (2.2)] .
- Must consume water with each dose of SUTAB and an additional 32 ounces of water after each dose.
- After breakfast, only clear liquids may be consumed until after the colonoscopy. Examples of clear liquids you can have are coffee or tea (no cream or non-dairy creamer), fruit juices (without pulp), gelatin desserts (no fruit or topping), water, chicken broth, clear soda (such as ginger ale).
- If preparation-related symptoms occur (e.g., nausea, bloating, cramping), pause or slow the rate of drinking the additional water until symptoms diminish.
- Do not take other laxatives while they are taking SUTAB.
- Do not drink milk or eat or drink anything colored red or purple.
- Do not drink alcohol.
- Administer oral medications at least one hour before starting each dose of SUTAB.
- If taking tetracycline or fluoroquinolone antibiotics, iron, digoxin, chlorpromazine, or penicillamine, take these medications at least 2 hours before and not less than 6 hours after administration of each dose of SUTAB.
- Complete all SUTAB tablets and required water at least two hours prior to colonoscopy.
- Contact their healthcare provider if they develop significant vomiting or signs of dehydration after taking SUTAB or if they experience cardiac arrhythmias or seizures [see Warnings and Precautions (5.1, 5.2, 5.3)] .
- Seek immediate medical care should signs or symptoms of a hypersensitivity reaction occur [see Warnings and Precautions (5.7)]

Manufactured by:

Braintree Laboratories, Inc.
270 Centre Street
Holbrook, MA 02343

Please see www.sebelapharma.com for patent information.
© Braintree Laboratories, Inc.

MEDICATION GUIDE

SUTAB®(Sootab)

(sodium sulfate, potassium sulfate and potassium chloride)

tablets, for oral use

Read and understand these Medication Guide Instructions at least 2 days beforeyour colonoscopy and again before you start taking SUTAB.

What is the most important information I should know about SUTAB?

SUTAB and other bowel preparations can cause serious side effects, including:

Serious loss of body fluid (dehydration) and changes in body salts (electrolytes) in your blood.

These changes can cause:

- abnormal heartbeats that can cause death.
- seizures.This can happen even if you have never had a seizure.
- kidney problems.

Your chance of having fluid loss and changes in body salts with SUTAB is higher if you:

- have heart problems.
- have kidney problems.
- take water pills (diuretics) or non-steroidal anti-inflammatory drugs (NSAIDs).

Tell your healthcare provider right away if you have any of these symptoms of a loss of too much body fluid (dehydration) while taking SUTAB:

- vomiting • urinating less often than normal
- dizziness • headache

See “What are the possible side effects of SUTAB?” for more information about side effects.

What is SUTAB?

SUTAB is a prescription medicine used by adults to clean the colon before a colonoscopy. SUTAB cleans your colon by causing you to have diarrhea. Cleaning your colon helps your healthcare provider see the inside of your colon more clearly during your colonoscopy.

It is not known if SUTAB is safe and effective in children.

Do nottake SUTAB if your healthcare provider has told you that you have:

- a blockage in your bowel (obstruction) or a problem with food moving too slowly through your intestines (ileus).
- an opening in the wall of your stomach or intestine (bowel perforation).
- a very dilated intestine (toxic colitis or toxic megacolon).
- problems with food and fluid emptying from your stomach (gastric retention).
- allergies to any ingredient in SUTAB. See the end of this Medication Guide for a complete list of ingredients in SUTAB.

Before taking SUTAB, tell your healthcare provider about all of your medical conditions, including if you:

- have heart problems.
- have stomach or bowel problems including ulcerative colitis.
- have problems with swallowing or gastric reflux.
- have a history of seizures.
- are withdrawing from drinking alcohol or from taking benzodiazepines.
- have a low blood salt (sodium) level.
- have kidney problems.
- are pregnant. It is not known if SUTAB will harm your unborn baby. Talk to your healthcare provider if you are pregnant.
- are breastfeeding or plan to breastfeed. It is not known if SUTAB passes into your breast milk. You and your healthcare provider should decide if you will take SUTAB while breastfeeding.

Tell your healthcare provider about all the medicines you take,including prescription and over-the-counter medicines, vitamins, and herbal supplements.

SUTAB may affect how other medicines work. Medicines taken by mouth may not be absorbed properly when taken within 1 hour before the start of each dose of SUTAB.

Especially tell your healthcare provider if you take:

- medicines for blood pressure or heart problems.
- medicines for kidney problems.
- medicines for seizures.
- water pills (diuretics).
- non-steroidal anti-inflammatory drugs (NSAIDs).
- medicines for depression or other mental health problems.
- laxatives. Do nottake other laxatives while taking SUTAB.

The following medicines should be taken at least 2 hours before starting each dose of SUTAB and not less than 6 hours after taking each dose of SUTAB:
• tetracycline • iron • chlorpromazine
• fluoroquinolone antibiotics • digoxin • penicillamine
Ask your healthcare provider or pharmacist for a list of these medicines if you are not sure if you are taking any of the medicines listed above.

Know the medicines you take. Keep a list of them to show your healthcare provider and pharmacist when you get a new medicine.

How should I take SUTAB?

See the Instructions for Use for dosing instructions. You must read, understand, and follow these instructions to take SUTAB the right way.

- Take SUTAB exactly as your healthcare provider tells you to take it.
- Each bottle contains 12 tablets and a drying agent (desiccant) canister to keep the tablets dry. Remove and throw away (discard) the drying agent (desiccant) canister from both bottles. Use the second bottle for the second dose on the morning of the colonoscopy.
- Each dose of SUTAB is 12 tablets that must be taken while drinking 16 ounces of water. Two doses of SUTAB (24 tablets) are required for a complete colonoscopy preparation.
- It is important for you to drink the additional 32 ounces of water after each dose to prevent fluid loss (dehydration).
- SUTAB is taken using the Split-Dosemethod. See the Instructions for Use for more information.
- All people taking SUTAB should follow these general instructions starting 1 day before your colonoscopy:
  o you can eat a low-residue breakfast. Low-residue foods include eggs, white bread, cottage cheese, yogurt, grits, coffee and tea.
  o after breakfast only drink clear liquids all day and the next day until 2 hours before your colonoscopy. Stop drinking all fluids at least 2 hours before the colonoscopy.
  o after taking the first dose of SUTAB (12 tablets) if you have any bloating or feeling like your stomach is upset, wait to take your second dose of 12 tablets until your stomach feels better.
- While taking SUTAB, do not:
  o take any other laxatives.
  o take any medicines by mouth (oral) within 1 hour of starting SUTAB.
  o eat solid foods, dairy such as milk, or drink alcohol.
  o eat or drink anything colored red or purple.

Contact your healthcare provider right awayif after taking SUTAB you have severe vomiting, signs of dehydration, abnormal heartbeats or seizures.

What are the possible side effects of SUTAB?

SUTAB can cause serious side effects, including:

- See What is the most important information I should know about SUTAB?
- Changes in certain blood tests.Your healthcare provider may do blood tests after you take SUTAB to check your blood for changes. Tell your healthcare provider if you have any symptoms of too much fluid loss, including:
  o vomiting o nausea o bloating
  o dizziness o stomach (abdominal) o headache
  o urinate less than usual cramping
  o trouble drinking clear liquid
- Heart problems. SUTAB may cause abnormal heartbeats.
- Seizures.
- Ulcers of the bowel or bowel problems (ischemic colitis).Tell your healthcare provider right away if you have severe stomach-area (abdominal) pain or rectal bleeding.
- Serious allergic reactions.Get medical help right away if you have any signs and symptoms of a serious allergic reaction while taking SUTAB, including:
  o Swelling of your hands, face o rash
  lips, mouth or tongue o severe itching
  o breathing problems o raised red patches on your skin

The most common side effects of SUTAB include:
• nausea • vomiting
• stomach-area swelling (abdominal distention) • upper stomach (abdominal) pain

These are not all the possible side effects of SUTAB.

Call your doctor for medical advice about side effects. You may report side effects to FDA at 1-800- FDA-1088.

How should I store SUTAB?

Each SUTAB bottle contains a drying agent (desiccant) canister to help keep the tablets dry (protect from moisture).

Store SUTAB at room temperature between 68°F to 77°F (20°C to 25°C).

Keep SUTAB and all medicines out of the reach of children.

General information about the safe and effective use of SUTAB.

Medicines are sometimes prescribed for purposes other than those listed in a Medication Guide. Do not use SUTAB for a condition for which it was not prescribed. Do not give SUTAB to other people, even if they are going to have the same procedure you are. It may harm them.

You can ask your pharmacist or healthcare provider for information that is written for health professionals.

What are the ingredients in SUTAB?

Active ingredients:sodium sulfate, magnesium sulfate, and potassium chloride.

Inactive ingredients: polyethylene glycol 8000, sodium caprylate, and ethylene glycol and vinyl alcohol graft copolymer

Manufactured by:

Braintree Laboratories, Inc.
270 Centre Street
Holbrook, MA 02343
For more information, go to www.braintreelabs.com or call 1-800-874-6756.

This Medication Guide has been approved by the U.S. Food and Drug Administration. Revised: 10/2023

Principal Display Panel Carton Label

NDC 52268-201-01

Please see www.sebelapharma.com for patent information.

SUTAB
(sodium sulfate, magnesium sulfate, and potassium chloride)
Tablets
1.479g/0.225g/0.188g

NOTE TO PHARMACIST:Inform patients to REMOVE AND DISCARD the DESICCANTfrom both medication bottles before SUTAB ingestion.

This carton contains:

2Bottles of 12 tablets each
116-ounce cup
1Patient booklet
Booklet includes:
1. Instructions for Use
2. Full Prescribing Information
3. Medication Guide

Both 12-tablet bottles are required for a complete preparation.

©2020 Braintree Laboratories Inc. All rights reserved. OCT 2023
SUT20101

Rx only

Braintree
A PART OF SEBELA PHARMACEUTICALS

Principal Display Panel Bottle Label

NDC 52268-200-01
Rx only

SUTAB
(sodium sulfate, magnesium sulfate, and potassium chloride)
Tablets
1.479g/0.225g/0.188g

REMOVE and DISCARD DESICCANT

This bottle contains 12 tablets and a desiccant.

Both 12-tablet bottles are required for a complete preparation.

Store at 25°C (77°F);
excursions permitted
15-30°C (59-86°F)

Recommended Dosage:
See full prescribing information

©2020 Manufactured by Braintree Laboratories, Inc. Braintree, MA